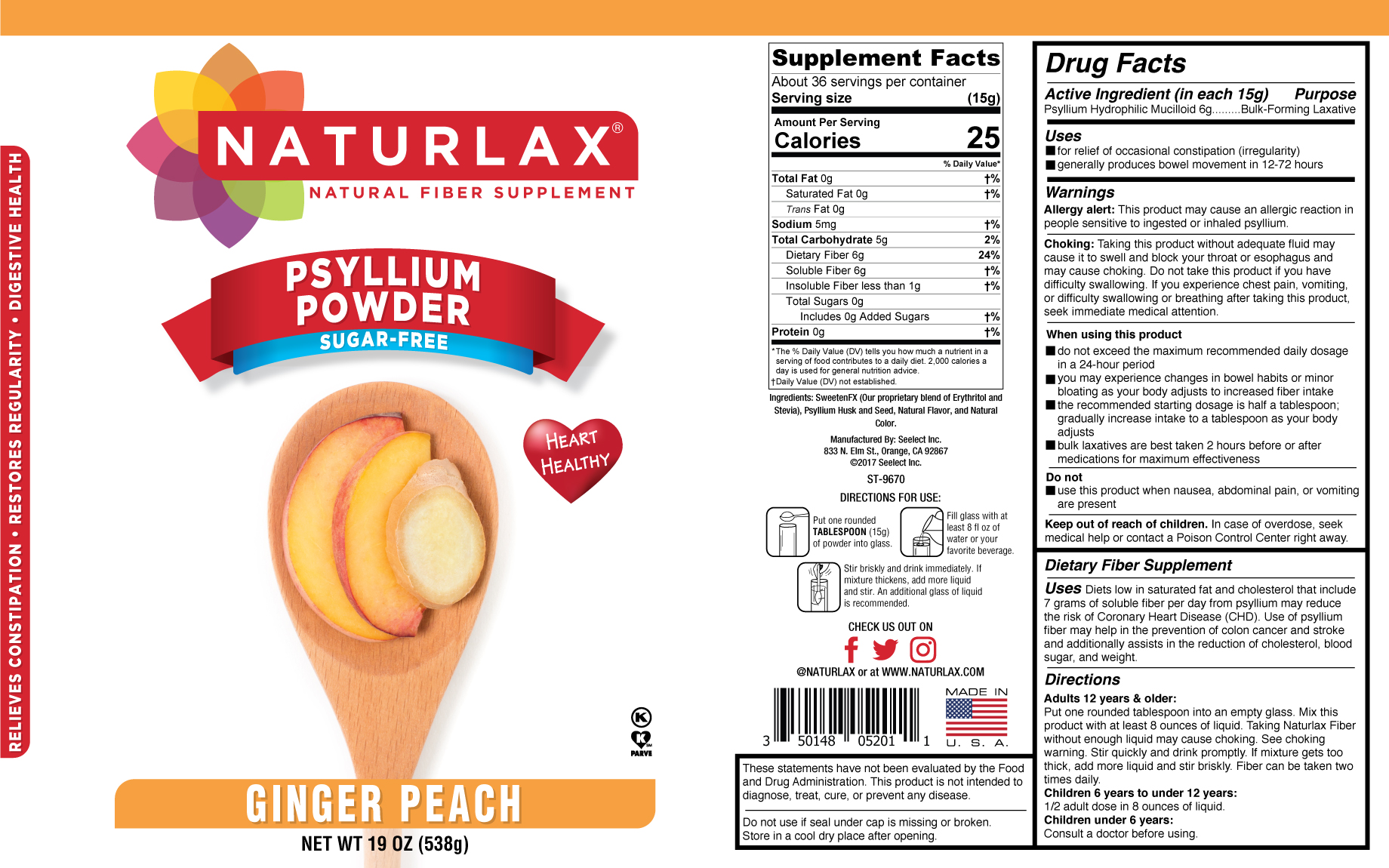 DRUG LABEL: Naturlax Ginger Peach Flavored Psyllium Fiber
NDC: 50148-052 | Form: POWDER
Manufacturer: Seelect Inc
Category: otc | Type: HUMAN OTC DRUG LABEL
Date: 20170518

ACTIVE INGREDIENTS: PSYLLIUM HUSK 15 g/99 g
INACTIVE INGREDIENTS: DEXTROSE

NATURALAX GINGER PEACH FLAVORED PSYLLIUM FIBER
Purpose section
keep out of reach of children section
Keep out of reach of children. In case of overdose, get
medical help or contact a Poison Control Center right away.
Naturlax Ginger Peach Flavored Psyllium Fiber
NET WT 3.5 OZ (99g)
NATURLAX®
NATURAL FIBER SUPPLEMENT
These statements have not been evaluated by the Food and
Drug Administration. This product is not intended to
diagnose, treat, cure, or prevent any disease.
Do not use if printed seal under cap is missing or broken.
Dietary Fiber Supplement
Dietary Fiber Supplement (continued)
Uses Psyllium Fiber is low in saturated fat and cholesterol
that include 7 grams of soluble fiber which reduces the risk
of Coronary Heart Diseases (CHD) by lowering cholesterol.
Directions
Adults 12 years & older:
Put one rounded tablespoon into an empty glass. Mix this
product with at least 8 ounces of liquid. Taking Naturlax Fiber
without enough liquid may cause choking. See choking
warning. Stir quickly and drink promptly. If mixture gets too
thick add more liquid and stir briskly. Fiber can be taken two
times daily.
Children 6 years to under 12 years:
1/2 adult dose in 8 ounces of liquid.
Children under 6 years:
Consult a doctor before using.

Naturlax Ginger Peach Flavored Psyllium Fiber

Indications & usage section

Purpose section

keep out of reach of children section

Keep out of reach of children. In case of overdose, get
medical help or contact a Poison Control Center right away.

Naturlax Ginger Peach Flavored Psyllium Fiber

NET WT 3.5 OZ (99g)
NATURLAX®
NATURAL FIBER SUPPLEMENT

These statements have not been evaluated by the Food and
Drug Administration. This product is not intended to
diagnose, treat, cure, or prevent any disease.
Do not use if printed seal under cap is missing or broken.

Dietary Fiber Supplement

Dietary Fiber Supplement (continued)
Uses Psyllium Fiber is low in saturated fat and cholesterol
that include 7 grams of soluble fiber which reduces the risk
of Coronary Heart Diseases (CHD) by lowering cholesterol.

Directions
Adults 12 years & older:
Put one rounded tablespoon into an empty glass. Mix this
product with at least 8 ounces of liquid. Taking Naturlax Fiber
without enough liquid may cause choking. See choking
warning. Stir quickly and drink promptly. If mixture gets too
thick add more liquid and stir briskly. Fiber can be taken two
times daily.
Children 6 years to under 12 years:
1/2 adult dose in 8 ounces of liquid.
Children under 6 years:
Consult a doctor before using.

Naturlax Ginger Peach Flavored Psyllium Fiber

Do not use laxative products when abdominal pain, nausea, or vomiting are present when using this product.

Naturlax Ginger Peach Flavored Psyllium Fiber

Psyllium Hydrophillic Mucilloid 6grams--- Bulking Forming Laxative

May Prevents Heart Disease

May Prevents Colon Cancer

May Prevents Stroke

May Reduces Cholesterol

May Reduces Blood Sugar

May Reduces Weight

May Promotes Digestive Health

May Promotes Regularity

May Promotes Oral Health

All Natural gluten-free dietary supplement

Relieves Constipation

No artificial Sweetener

Natural Colors high in antioxidants

Naturlax Ginger Peach Flavored Psyllium Fiber

Psyllium Hydrophillic Mucilloid

Naturlax Ginger Peach Flavored Psyllium Fiber

Inactive Ingredient Dextrose

Naturlax Ginger Peach Flavored Psyllium Fiber

Directions
Adults 12 years & older:
Put one rounded tablespoon into an empty glass. Mix this
product with at least 8 ounces of liquid. Taking Naturlax Fiber
without enough liquid may cause choking. See choking
warning. Stir quickly and drink promptly. If mixture gets too
thick add more liquid and stir briskly. Fiber can be taken two
times daily.
Children 6 years to under 12 years:
1/2 adult dose in 8 ounces of liquid.
Children under 6 years:
Consult a doctor before using.

Naturlax Ginger Peach Flavored Psyllium Fiber

Serving Size 1 tablespoon (15grams) Consist of 6 grams of Bulk forming Fiber and 7 grams of Soluble Fiber

Naturlax Ginger Peach Flavored Psyllium Fiber

Indications & usage section

Purpose section

keep out of reach of children section

Keep out of reach of children. In case of overdose, get
medical help or contact a Poison Control Center right away.

Naturlax Ginger Peach Flavored Psyllium Fiber

NET WT 3.5 OZ (99g)
NATURLAX®
NATURAL FIBER SUPPLEMENT

These statements have not been evaluated by the Food and
Drug Administration. This product is not intended to
diagnose, treat, cure, or prevent any disease.
Do not use if printed seal under cap is missing or broken.

Dietary Fiber Supplement

Dietary Fiber Supplement (continued)
Uses Psyllium Fiber is low in saturated fat and cholesterol
that include 7 grams of soluble fiber which reduces the risk
of Coronary Heart Diseases (CHD) by lowering cholesterol.

Directions
Adults 12 years & older:
Put one rounded tablespoon into an empty glass. Mix this
product with at least 8 ounces of liquid. Taking Naturlax Fiber
without enough liquid may cause choking. See choking
warning. Stir quickly and drink promptly. If mixture gets too
thick add more liquid and stir briskly. Fiber can be taken two
times daily.
Children 6 years to under 12 years:
1/2 adult dose in 8 ounces of liquid.
Children under 6 years:
Consult a doctor before using.